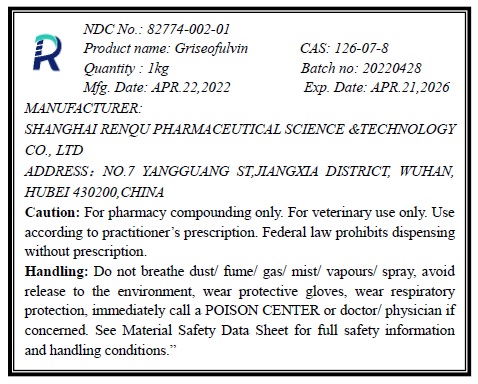 DRUG LABEL: Griseofulvin
NDC: 82774-002 | Form: POWDER
Manufacturer: Shanghai Renqu Pharmaceutical Science & Technology Co., Ltd.
Category: other | Type: BULK INGREDIENT - ANIMAL DRUG
Date: 20220618

ACTIVE INGREDIENTS: GRISEOFULVIN 1 kg/1 kg

Griseofulvin